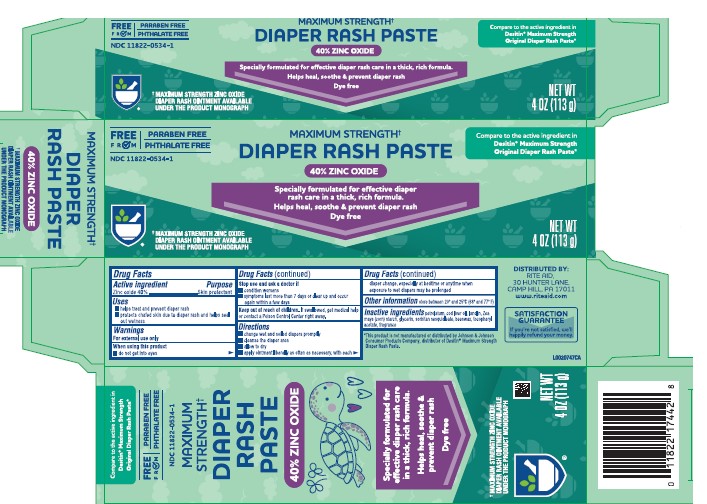 DRUG LABEL: Zinc Oxide
NDC: 11822-0534 | Form: OINTMENT
Manufacturer: Rite Aid Corporation
Category: otc | Type: HUMAN OTC DRUG LABEL
Date: 20260130

ACTIVE INGREDIENTS: ZINC OXIDE 400 mg/1 g
INACTIVE INGREDIENTS: COD LIVER OIL; LANOLIN; STARCH, CORN; GLYCERIN; SORBITAN SESQUIOLEATE; YELLOW WAX; TOCOPHEROL; PETROLATUM

Rite Aid 020.002/020AC-AD
Diaper Rash Paste

Active ingredient

Zinc oxide 40%

Purpose

Skin Protectant

Uses

• helps treat and prevent diaper rash
• protects chafed skin due to the diaper rash and helps seal out wetness

Warnings

For external use only

When using this product

- do not get into eyes

Stop use and ask a doctor if

- condition worsens
- symptoms last more than 7 days or clear up and occur again within a few days

Keep out of reach of children.

If swallowed, get medical help or contact a Poison Control Center right away.

Directions

• change wet and soiled diapers promptly
• cleanse the diaper area
• allow to dry
• apply ointment liberally as often as necessary, with each diaper change, especially at bedtime or anytime when exposure to wet diapers may be prolonged

Other information

• store between 20⁰ and 25⁰C (68⁰ and 77⁰F)

Inactive ingredients

petrolatum, cod liver oil, lanolin, Zea mays (corn) starch, glycerin, sorbitan sesquioleate, beeswax, tocopheryl acetate, fragrance

Disclaimer

*This product not manufactured or disturbed by Johnson & Johnson Consumer Products Company, distributor of DesitinMaximum Strength Diaper Rash Paste.

ADVERSE REACTION

DISTRIBUTED BY:

RITE AID

30 HUNTER LANE

CAMP HILL, PA 17011

www.riteaid.com

SATISFACTION GUARENTEE

if you're not satisfied, we'll happily refund your money.

principal display panel

FREE FROM

PARABEN FREE

PHTHALATE FREE

NDC 11822-0534-1

MAXIMUM STRENGTH†

DIAPER RASH PASTE

40% ZINC OXIDE

Specially formulated for effective diaper rash care in a thick, rich formula

Helps heal, soothe & prevent diaper rash

Dye free

†MAXIMUM STRENGTH ZINC OXIDE DIAPER RASH OINTMENT AVAILABLE UNDER THE PRODOCT MONOGRAPH

Compare to the active ingredient in Destin®Maximum Strength Original Ciaper Rash Paste*

NET WT 4OZ (113g)